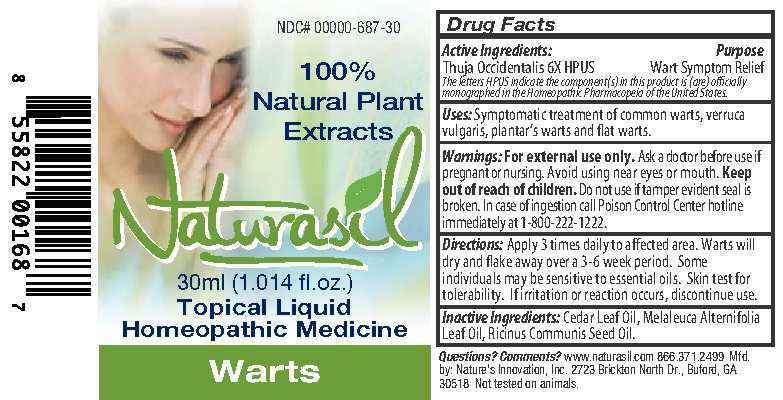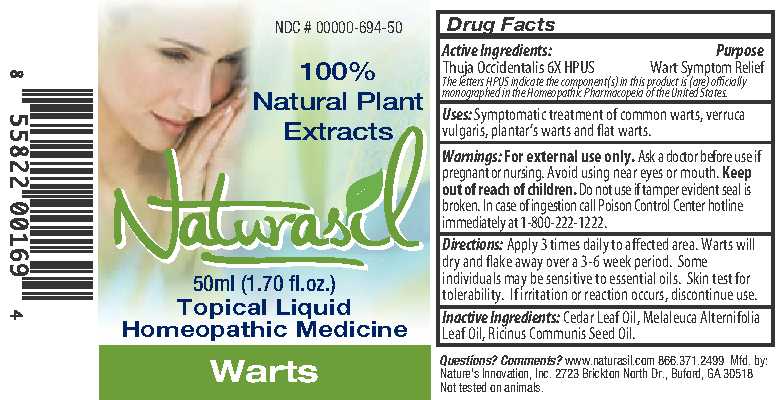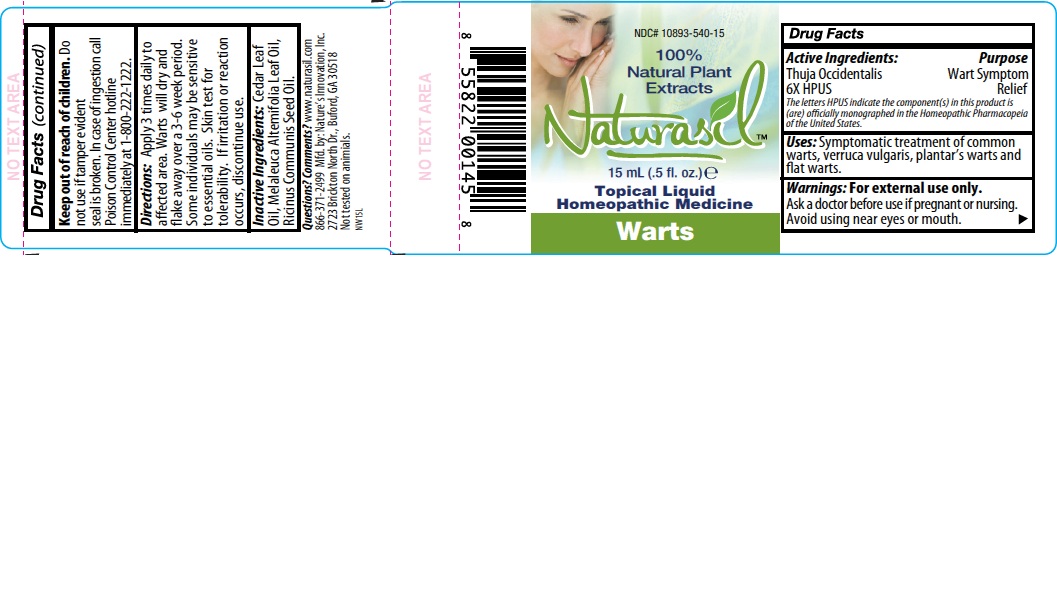 DRUG LABEL: Naturasil
NDC: 10893-540 | Form: LIQUID
Manufacturer: Nature's Innovation, Inc.
Category: homeopathic | Type: HUMAN OTC DRUG LABEL
Date: 20250725

ACTIVE INGREDIENTS: THUJA OCCIDENTALIS LEAFY TWIG 6 [hp_X]/1 mL
INACTIVE INGREDIENTS: CEDAR LEAF OIL; TEA TREE OIL; CASTOR OIL

Warts Labeling

Drug Facts

Active Ingredients:

Thuja Occidentalis 6X HPUS

DESCRIPTION

The letters HPUS indicate the component(s) in this product is (are) officially monographed in the Homeopathic Pharmacopeia of the United States.

Uses

Uses: Symptomatic treatment of common warts, verruca vulgaris, plantar's warts and flat warts.

Warnings

Warnings: For external use only.

Ask a doctor before use if pregnant or nursing.

WHEN USING

Avoid use near eyes or mouth.

Keep out of reach of children.

Do not use if tamper evident seal is broken.

OTHER SAFETY INFORMATION

In case of ingestion call Poison Control Center hotline at 1-800-222-1222.

Directions

Directions: Apply 3 times daily to affected area. Warts will dry and flake away over a 3-6 week period. Some individuals may be sensitive to essential oils. Skin test for tolerability. If irritation or reaction occurs, discontinue use.

Inactive Ingredients

Inactive Ingredients: Cedar Leaf oil, Melaleuca Alternifolia Leaf Oil, Ricinus Communis Seed Oil.

Questions

Questions? Comments?
www.naturasil.com 1-866-371-2499
Mfd. by: Nature's Innovation, Inc.,
2723 Brickton North Dr., Buford, GAA 30518
Not tested on animials.

Purpose

Wart Symptom Relief

PACKAGE LABEL

NDC#
100%
Natural Plant
Extracts
Naturasil
10ml (.34 fl. oz.)
Topical Liquid
Homeopathic Medicine
Warts